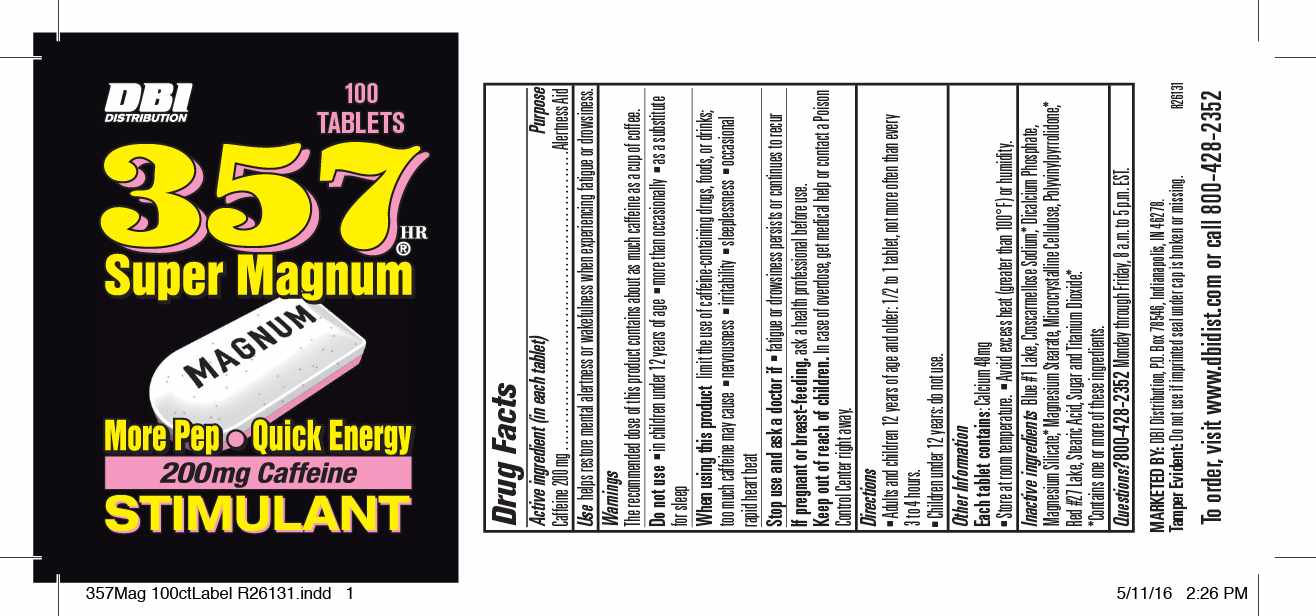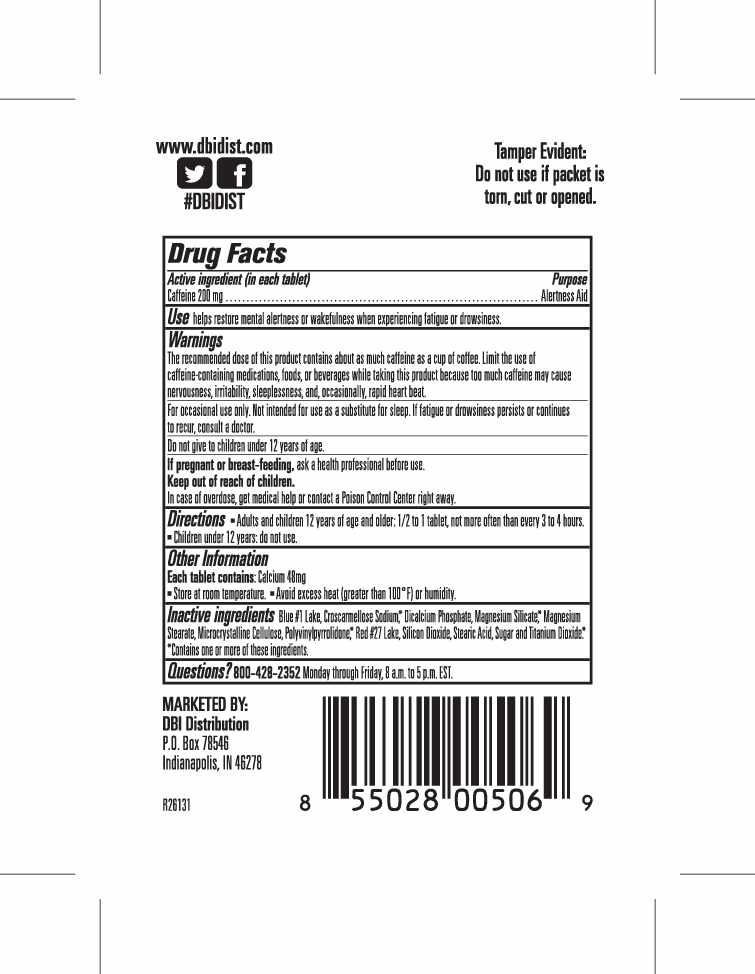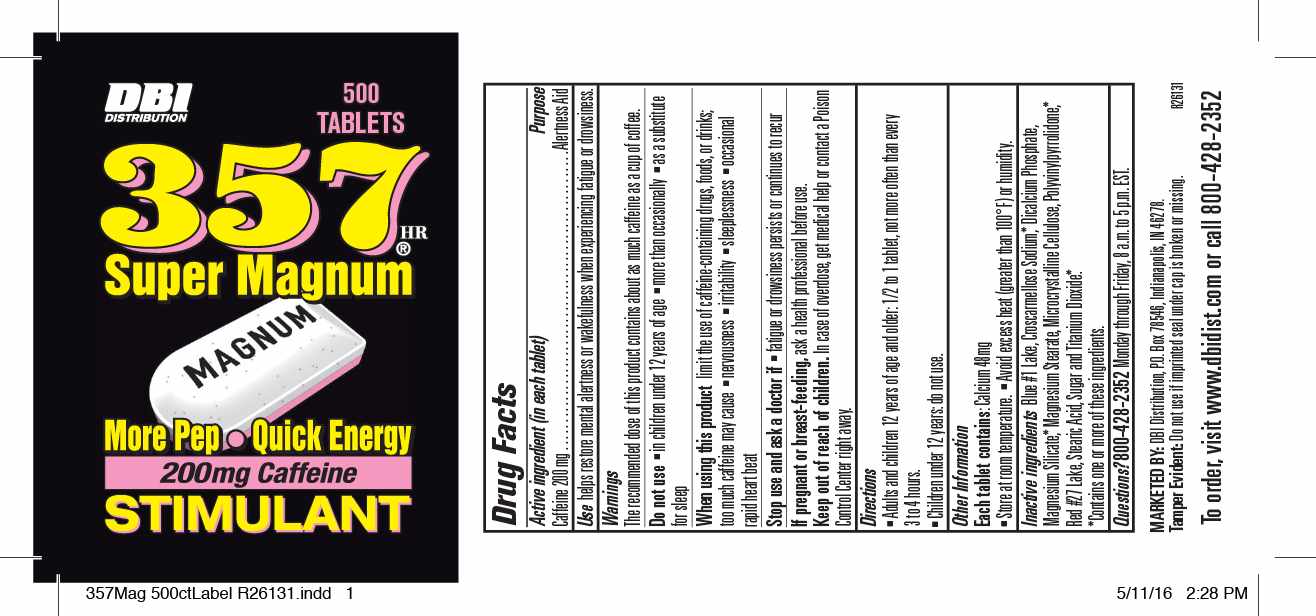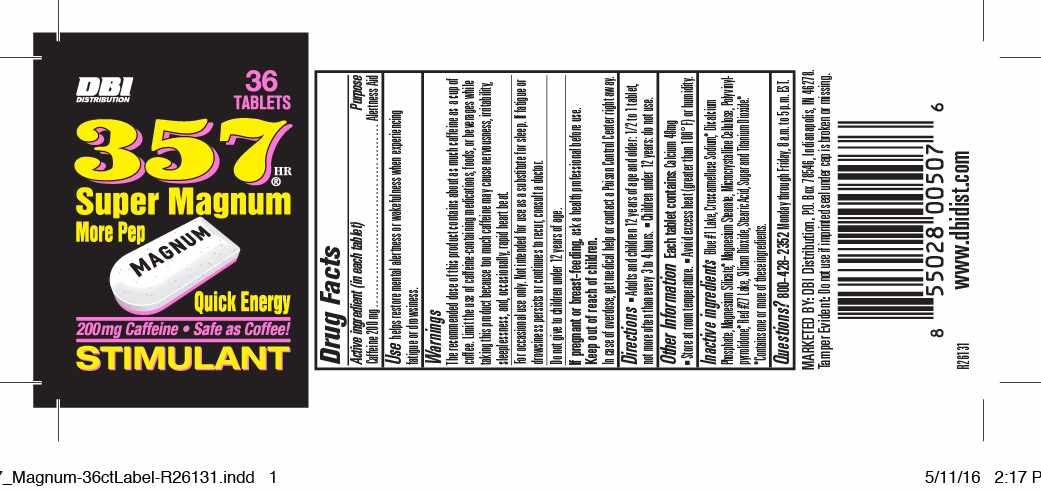 DRUG LABEL: 357 Super Magnum
NDC: 70682-941 | Form: TABLET, MULTILAYER
Manufacturer: King Richard Promotions dba DBI 
Category: otc | Type: HUMAN OTC DRUG LABEL
Date: 20160519

ACTIVE INGREDIENTS: CAFFEINE 200 1/1 1
INACTIVE INGREDIENTS: D&C RED NO. 27; DIBASIC CALCIUM PHOSPHATE DIHYDRATE; FD&C BLUE NO. 1; MAGNESIUM STEARATE; CELLULOSE, MICROCRYSTALLINE; POVIDONE; SILICON DIOXIDE; STEARIC ACID; SUCROSE

357 Super Magnum

Active ingredient (in each tablet)

Caffeine 200mg

Purpose: Alertness Aid

INDICATIONS AND USAGE

Use: Helps restore mental alertness or wakefulness when experiencing fatigue or drowsiness.

WARNINGS

Warnings: The recommended dose of this product contains about as much caffeine as a cup of coffee. Limit the use of caffeine-containing medications, foods, or beverages while taking this product because too much caffeine may cause nervousness, irritability, sleeplessness, and, occasionally, rapid heartbeat.

For occasional use only.Not intended for use as a substitute for sleep. If fatigue or drowsiness persists or continues to recur, consult a doctor.

Do not give to children under 12 years of age.

PREGNANCY OR BREAST FEEDING

If pregnant or breastfeeding, ask a health professional before use.

Keep out of the reach of children.

OVERDOSAGE

In case of overdose, get medical help or contact a Poison Control Center immediately.

DOSAGE AND ADMINISTRATION

Directions: Adults and children 12 years of age or older: 1/2 to 1 tablet, not more often than every 3-4 hours.

Children under 12 years: do not use.

Other Information:

Each tablet contains: Calcium 48mg

Store at room temperature.

Avoid excess heat (greater than 100°F) or humidity.

INACTIVE INGREDIENT

Inactive ingredients: blue #1 lake, croscarmellose sodium*, dicalcium phosphate , magnesium silicate*, magnesium stearate, microcrystalline cellulose, polyvinylpyrrolidone, red #27 lake, silicon dioxide, stearic acid, sugar, and titanium dioxide*

*Contains one or more of these ingredients

Questions?

Call toll-free 1-800-428-2352 Monday through Friday, 8a.m. to 5p.m. EST.